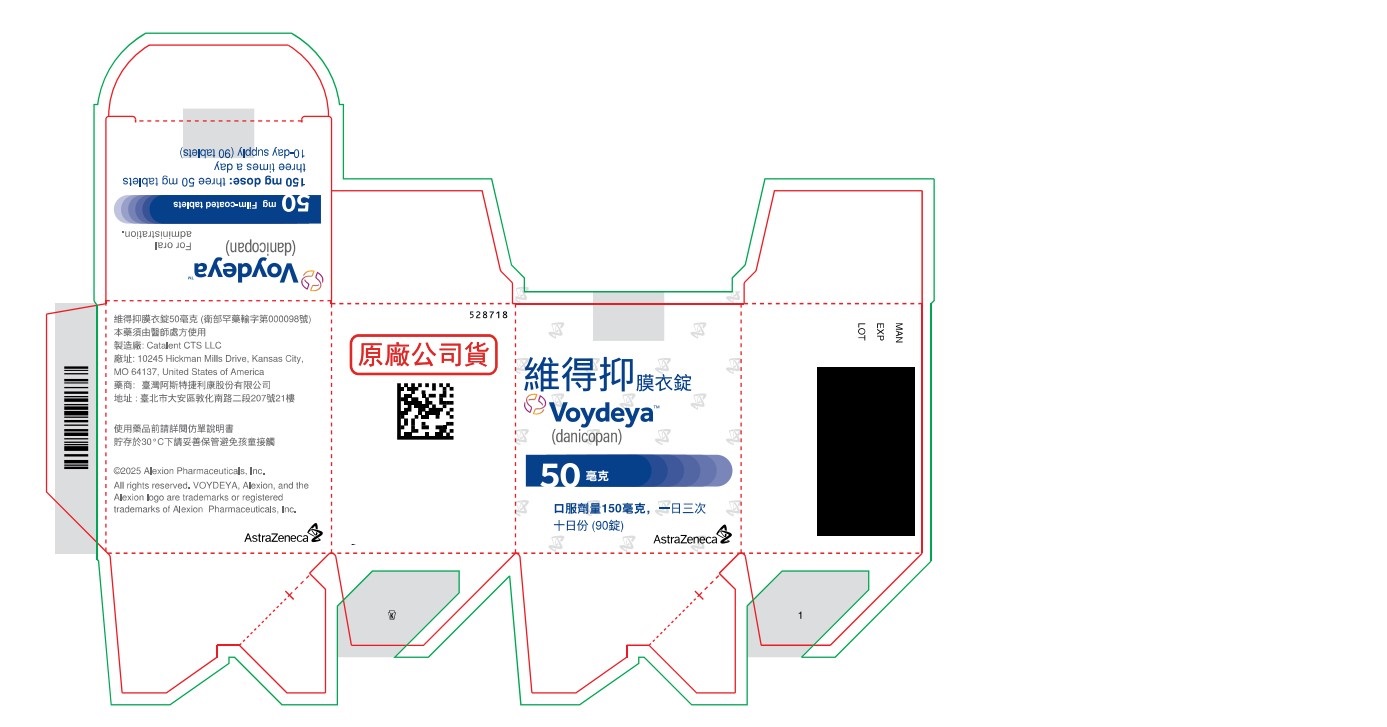 DRUG LABEL: Voydeya
NDC: 11014-0739 | Form: TABLET, FILM COATED
Manufacturer: Catalent Pharma Solutions, LLC
Category: prescription | Type: HUMAN PRESCRIPTION DRUG LABEL
Date: 20251127

ACTIVE INGREDIENTS: DANICOPAN 50 mg/1 1

Voydeya 50mg Tablets

Voydeya 50 mg tablets (11014-0739-1)

Carton-Label